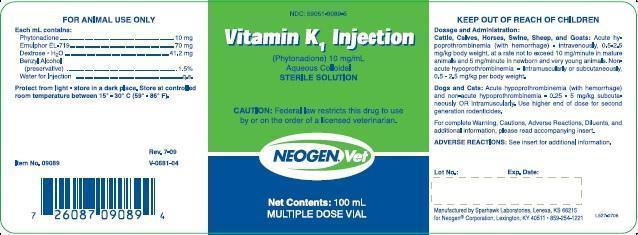 DRUG LABEL: Vitamin K1 Injectable
NDC: 59051-9089 | Form: INJECTION
Manufacturer: Neogen Corporation - Nandino
Category: animal | Type: PRESCRIPTION ANIMAL DRUG LABEL
Date: 20121127

ACTIVE INGREDIENTS: PHYTONADIONE 10 mg/1 mL
INACTIVE INGREDIENTS: PEG-40 CASTOR OIL; DEXTROSE; BENZYL ALCOHOL; Water

NeogenVet Vitamin K1 Injection

FOR ANIMAL USE ONLY

Each mL contains:

Phytonadione..................................10 mg

Emulphor EL-719.............................70 mg

Dextrose H2O...............................41.2 mg

Benzyl Alcohol (preservative)............1.5%

Water for Injection..............................q.s.

STORAGE AND HANDLING

Protect from light - store in a dark place. Store at controlled room temperature between 15°-30°C (59°-86°F).

Rev. 7-09

V-0681-04

Item No. 09089

Principal Display Panel Vitamin K1 Injection 100 mL

NDC: 59051-9089-5

Vitamin K1 Injections

(Phytonadione) 10 mg/mL

Aqueous Colloidal

STERILE SOLUTION

CAUTION: Federal law restricts this drug to use by or on the order of a licensed veterinarian.

NEOGEN.Vet

Net Contents: 100 mL

MULTIPLE DOSE VIAL

KEEP OUT OF REACH OF CHILDREN

Dosage and Administration:

Cattle, Calves, Horses, Swine, Sheep, and Goats: Acute hypotrothrombinemia (with hemorrhage): intravenously, 0.5-2.5 mg/kg body weight, at a rate not to exceed 10 mg/minute in mature animals and 5 mg/minute in newborn and very young animals. Non-acute hypoprothrombinemia: intramuscularly or subcutaneously, 0.5-2.5 mg/kg per body weight.

Dogs and Cats: Acute hypoprothrombinemia (with hemorrhage) and non-acute hypoprothrombinemia-- 0.25-5 mg/kg subcutaneously OR intramuscularly. Use higher end dose for second generation rodenticides.

ADVERSE REACTIONS: See insert for additional information.

Manufactured by Sparhawk laboratories, Lenexa, KS 66215

for Neogen®Corporation, Lexington, KY 40511 859-254-1221

Package Insert

VITAMIN K1

(Phytonadione)

Injection

Vitamin K Injection

(Phytonadione)

Aqueous Colloidal Solution of Vitamin K1

___________________________________________________________________________________________________________

WARNING---INTRAVENOUS USE:

Severe reactions, including fatalities, have occurred during and immediately after INTRAVENOUS injection of Phytonadione, even when precautions have been taken to dilute the Vitamin K1 and to avoid rapid infusion. Typically, these severe reactions have resembled hypersensitivity or anaphylaxis, including shock and cardiac and or respiratory arrest. Some animals have exhibited these severe reactions on receiving Vitamin K1 Injection for the first time.

Therefore, the intravenous route should be restricted to those situations where other routes are not feasible and the serious risk involved is considered justified.

See ADVERSE REACTION section for possible Intramuscular and Subcutaneous reactions.

_____________________________________________________________________________________________________________

DESCRIPTION: Vitamin K1 Injection is a yellow, sterile acqueous colloidal solution of Vitamin K1 (phytonadione), available for injection by the intravenous, intramuscular and subcutaneous routes. Each mL contains:

Phytonadione...................................10 mg

Inactive Ingredients

Emulphor EL-719..............................70 mg

Dextrose H2O...............................41.2 mg

Water...................................................q.s.

Added as a preservative

Benzyl Alcohol....................................1.5%

ACTIONS: Vitamin K1 Injection, an aqueous colloidal solution of Vitamin K1 for parenteral injection, possesses the same type and degree of activity as does naturally occurring Vitamin K. The primary function of vitamin K is to stimulate the production via the liver of active prothrombin from a precursor protein. The mechanism by which vitamin K promotes formation of prothrombin at the molecular level has not been established. The action of the aqueous colloidal solution, when administered intravenously, is generally detectable within an hour or two and hemorrhage is usually controlled within 3 to 6 hours. A normal prothrombin level may often be obtained in 12 to 14 hours.

INDICATIONS: Vitamin K1 Injection is indicated in cattle, calves, horses, swine, sheep, goats, dogs and cats to counter Hypoprothrombinemia induced by ingestion of coumarin-based compounds, common ingredients in commercial rodenticides. Vitamin K1 Injection is also indicated to counter hypoprothrombinemia caused by consumption of Bishydroxycoumarin found in spoiled and moldy sweet clover.

NOTE: Regualr determinations of prothrombin time response should be performed to guide in the initial and subsequent administration of Vitamin K1 Injection. The dosage should be adjusted accordingly.

CONTRAINDICATIONS: Hypersensitivity to any component of this medication.

WARNINGS: An immediate coagulant effect should not be expected after administration of phytonadione. A minimum of 1 to 2 hours is required for measurable improvement in the prothrombin time. Whole blood or component therapy may be necessary if the bleeding is severe.

Phytonadione will not counteract the anticoagulant action of heparin.

Repeated large doses of vitamin K are not warranted in hepatic disease if the response to the initial therapy is unsatisfactory. Failure to respond to vitamin K may indicate that the condition being treated is inherently unresponsive to vitamin K.